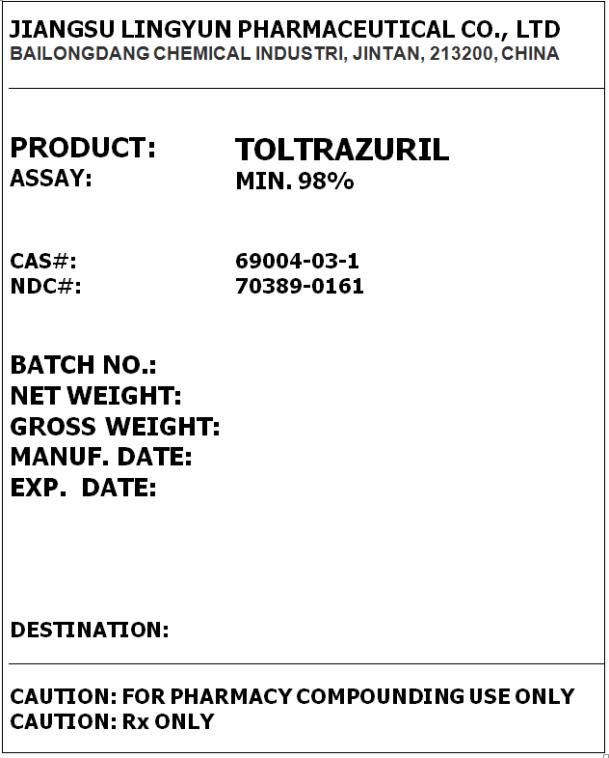 DRUG LABEL: Toltrazuril
NDC: 70389-0161 | Form: POWDER
Manufacturer: Jiangsu Lingyun Pharmaceutical Co., Ltd
Category: other | Type: BULK INGREDIENT
Date: 20161104

ACTIVE INGREDIENTS: TOLTRAZURIL 1 kg/1 kg

Toltrazuril

PRINCIPAL DISPLAY PANEL – BULK PRODUCT

JIANGSU LINGYUN PHARMACEUTICAL CO., LTD
BAILONGDANG CHEMICAL INDUSTRI, JINTAN, 213200, CHINA

PRODUCT: TOLTRAZURIL
ASSAY: MIN. 98%

CAS#: 69004-03-1
NDC#: 70389-0161

CAUTION: FOR PHARMACY COMPOUNDING USE ONLY
CAUTION: Rx ONLY